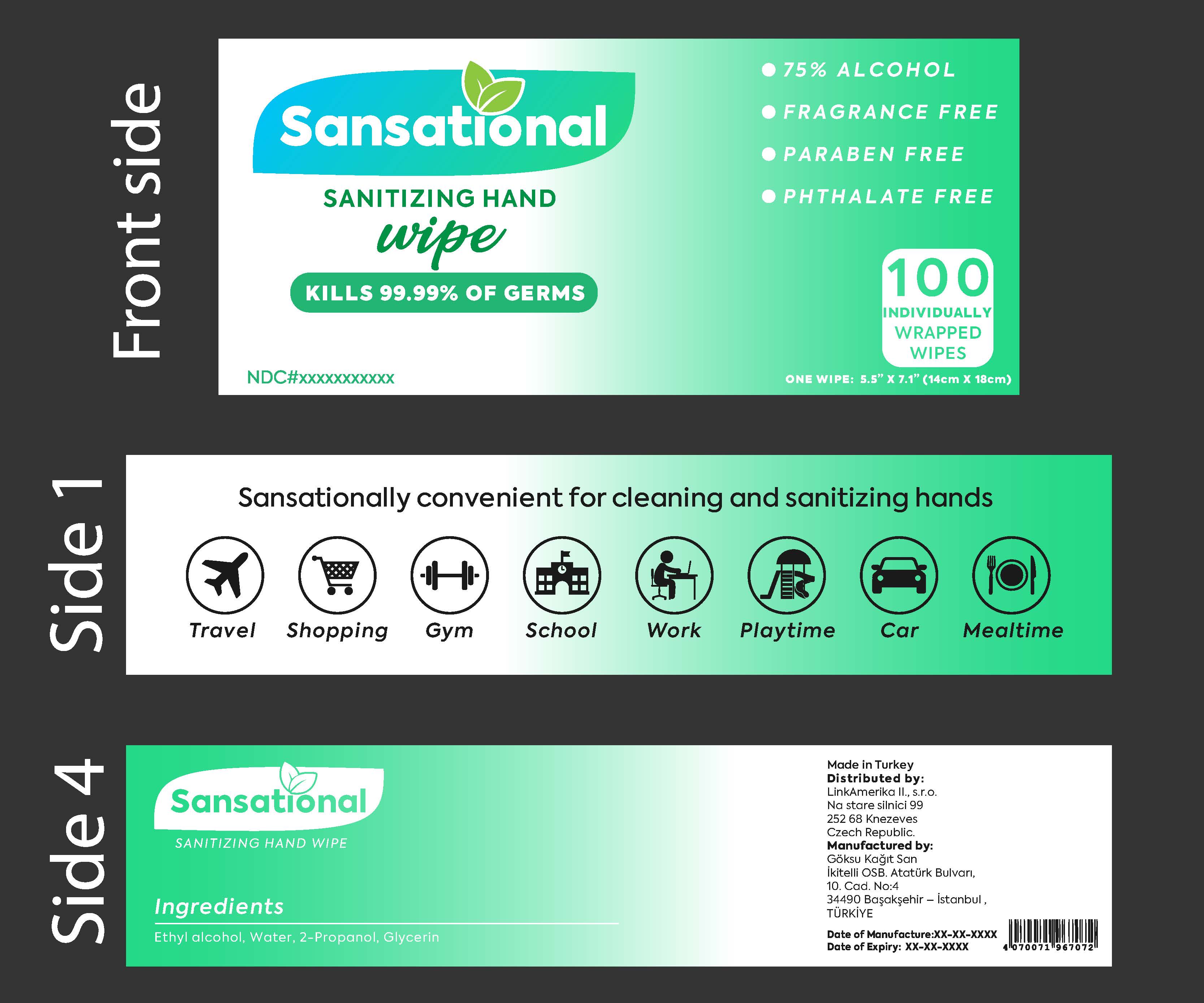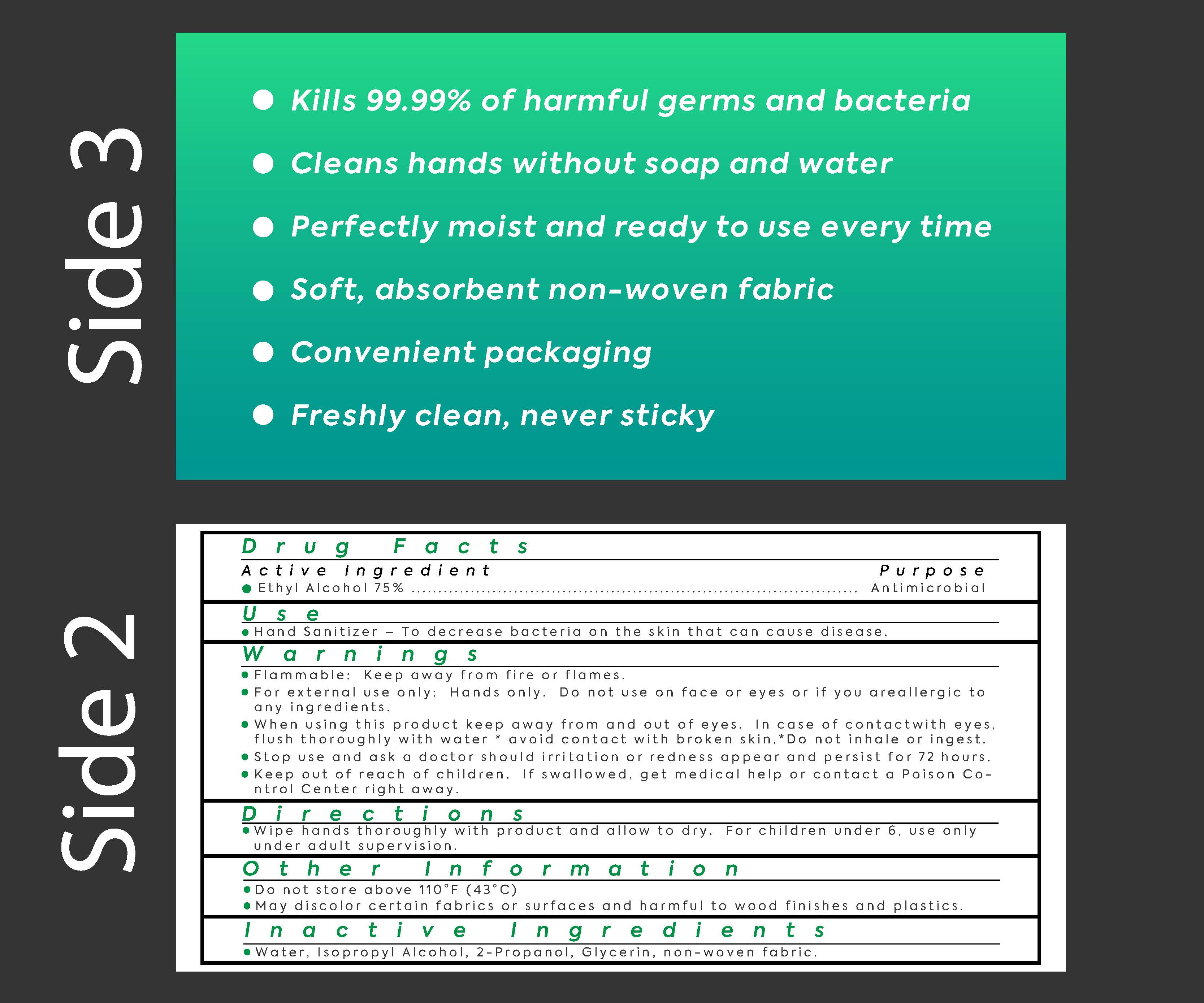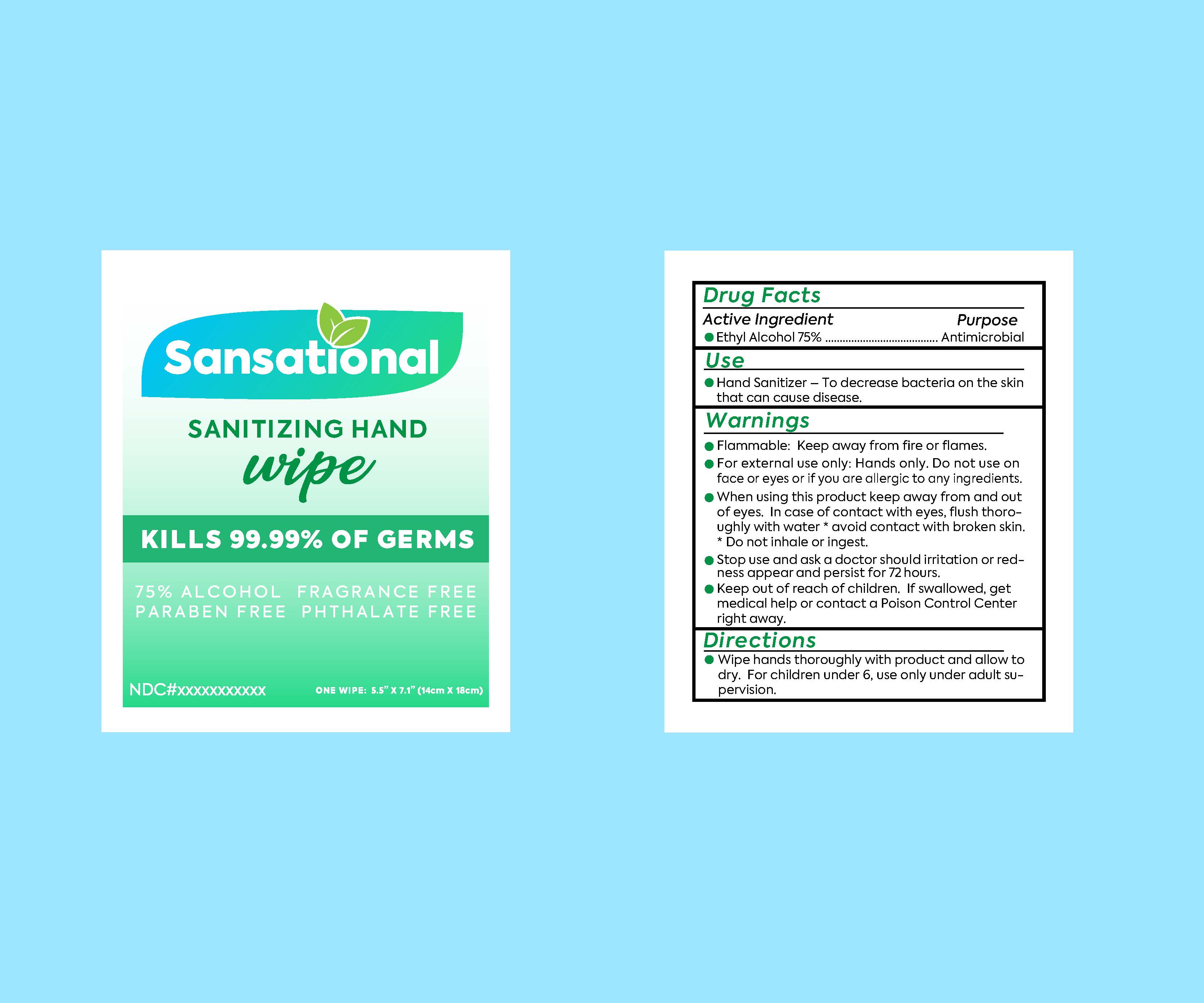 DRUG LABEL: ALCOHOL WIPES
NDC: 79509-001 | Form: CLOTH
Manufacturer: GOKSU KAGIT SANAYI VE TICARET LIMITED SIRKETI
Category: otc | Type: HUMAN OTC DRUG LABEL
Date: 20200710

ACTIVE INGREDIENTS: ALCOHOL 75 U/100 U
INACTIVE INGREDIENTS: GLYCERIN; WATER; ISOPROPYL ALCOHOL

Active Ingredient(s)

Alcohol 75% v/v. Purpose: Antiseptic

Purpose

Antiseptic, Hand Sanitizer

Use

Hand Sanitizer to help reduce bacteria that potentially can cause disease. For use when soap and water are not available.

Warnings

For external use only. Flammable. Keep away from heat or flame

Do not use

- in children less than 2 months of age
- on open skin wounds

When using this product keep out of eyes, ears, and mouth. In case of contact with eyes, rinse eyes thoroughly with water.
Stop use and ask a doctor if irritation or rash occurs. These may be signs of a serious condition.
Keep out of reach of children. If swallowed, get medical help or contact a Poison Control Center right away.

Stop use and ask a doctor if irritation or rash occurs. These may be signs of a serious condition.

Keep out of reach of children. If swallowed, get medical help or contact a Poison Control Center right away.

Directions

- Place enough product on hands to cover all surfaces. Rub hands together until dry.
- Supervise children under 6 years of age when using this product to avoid swallowing.

Other information

- Store between 15-30C (59-86F)
- Avoid freezing and excessive heat above 40C (104F)

Inactive ingredients

glycerin,water,isopropyl alcohol,2-proponal

Package Label - Principal Display Panel

1 Box 79509-001-02

100 U 79509-001-01